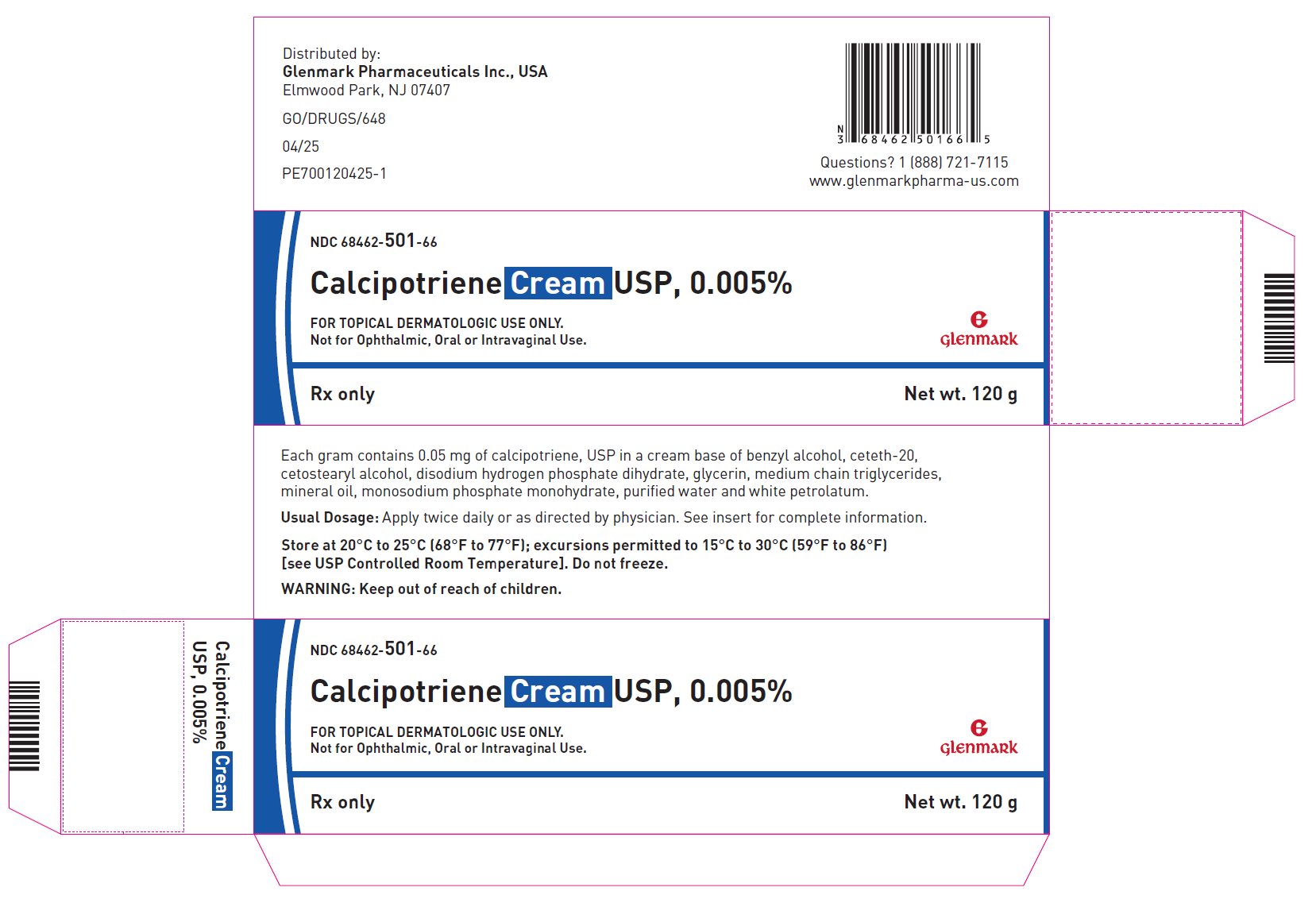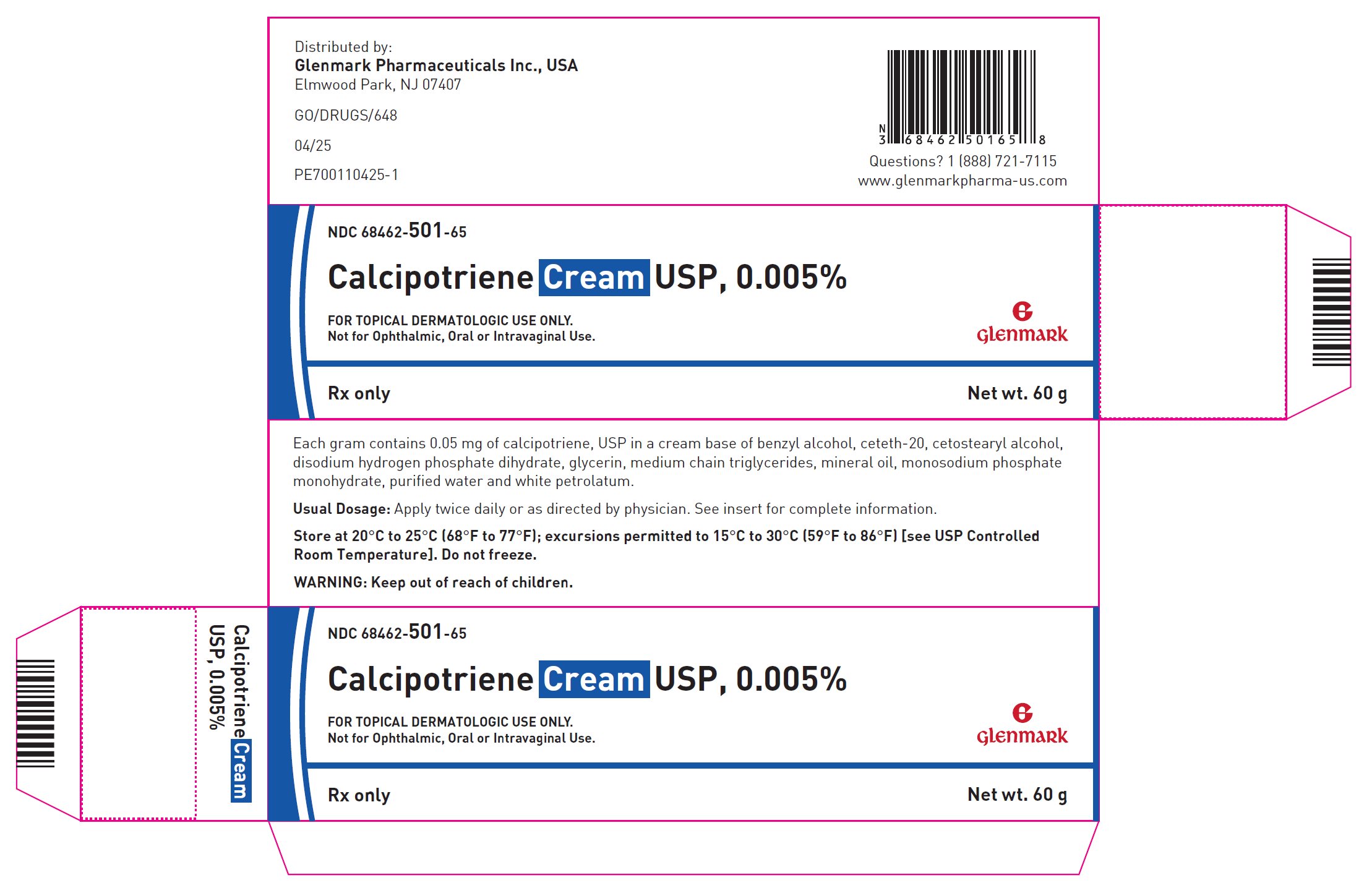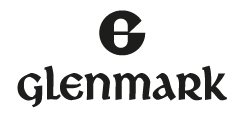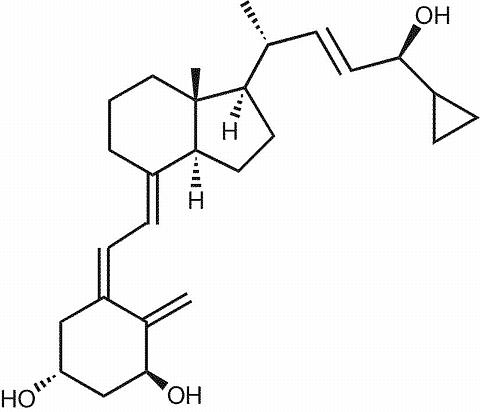 DRUG LABEL: calcipotriene
NDC: 68462-501 | Form: CREAM
Manufacturer: Glenmark Pharmaceuticals Inc.,USA
Category: prescription | Type: HUMAN PRESCRIPTION DRUG LABEL
Date: 20251027

ACTIVE INGREDIENTS: CALCIPOTRIENE 50 ug/1 g
INACTIVE INGREDIENTS: BENZYL ALCOHOL; CETOSTEARYL ALCOHOL; CETETH-20; SODIUM PHOSPHATE, DIBASIC, DIHYDRATE; GLYCERIN; MEDIUM-CHAIN TRIGLYCERIDES; MINERAL OIL; SODIUM PHOSPHATE, MONOBASIC, MONOHYDRATE; WATER; PETROLATUM

CALCIPOTRIENE CREAM USP, 0.005%

Rx only

FOR TOPICAL DERMATOLOGIC USE ONLY.

Not for Ophthalmic, Oral or Intravaginal Use.

DESCRIPTION

Calcipotriene Cream USP, 0.005% contains calcipotriene, USP, a synthetic vitamin D3 derivative, for topical dermatological use.

Chemically, calcipotriene, USP is (5Z,7E,22E,24S)-24-cyclopropyl-9,10-secochola-5,7,10(19),22-tetraene-1α,3β,24-triol, with the empirical formula C27H40O3, a molecular weight of 412.62 and the following structural formula:

Calcipotriene, USP is a white or almost white crystalline powder. Calcipotriene Cream USP, 0.005% contains 50 mcg/g anhydrous calcipotriene, USP in a cream base of benzyl alcohol, ceteth-20, cetostearyl alcohol, disodium hydrogen phosphate dihydrate, glycerin, medium chain triglycerides, mineral oil, monosodium phosphate monohydrate, purified water and white petrolatum.

CLINICAL PHARMACOLOGY

In humans, the natural supply of vitamin D depends mainly on exposure to the ultraviolet rays of the sun for conversion of 7-dehydrocholesterol to vitamin D3 (cholecalciferol) in the skin. Calcipotriene is a synthetic analog of vitamin D3.

Clinical studies with radiolabelled calcipotriene ointment indicate that approximately 6% (± 3%, SD) of the applied dose of calcipotriene is absorbed systemically when the ointment is applied topically to psoriasis plaques, or 5% (± 2.6%, SD) when applied to normal skin, and much of the absorbed active is converted to inactive metabolites within 24 hours of application. Systemic absorption of the cream has not been studied.

Vitamin D and its metabolites are transported in the blood, bound to specific plasma proteins. The active form of the vitamin, 1,25-dihydroxy vitamin D3 (calcitriol), is known to be recycled via the liver and excreted in the bile. Calcipotriene metabolism following systemic uptake is rapid, and occurs via a similar pathway to the natural hormone.

CLINICAL STUDIES

Adequate and well-controlled trials of patients treated with calcipotriene cream have demonstrated improvement usually beginning after 2 weeks of therapy. This improvement continued with approximately 50% of patients showing at least marked improvement in the signs and symptoms of psoriasis after 8 weeks of therapy, but only approximately 4% showed complete clearing.

INDICATIONS AND USAGE

Calcipotriene cream, 0.005%, is indicated for the treatment of plaque psoriasis. The safety and effectiveness of topical calcipotriene in dermatoses other than psoriasis have not been established.

CONTRAINDICATIONS

Calcipotriene cream is contraindicated in those patients with a history of hypersensitivity to any of the components of the preparation. It should not be used by patients with demonstrated hypercalcemia or evidence of vitamin D toxicity. Calcipotriene cream should not be used on the face.

WARNINGS

Contact dermatitis, including allergic contact dermatitis, has been observed with the use of calcipotriene cream.

PRECAUTIONS

General

Use of calcipotriene cream may cause transient irritation of both lesions and surrounding uninvolved skin. If irritation develops, calcipotriene cream should be discontinued.

For external use only. Keep out of the reach of children. Always wash hands thoroughly after use.

Reversible elevation of serum calcium has occurred with use of topical calcipotriene. If elevation in serum calcium outside the normal range should occur, discontinue treatment until normal calcium levels are restored.

Information for Patients

Patients using calcipotriene cream should receive the following information and instructions:

1. This medication is to be used only as directed by the physician. It is for external use only. Avoid contact with the face or eyes. As with any topical medication, patients should wash their hands after application.
2. This medication should not be used for any disorder other than that for which it was prescribed.
3. Patients should report to their physician any signs of adverse reactions.
4. Patients that apply calcipotriene cream to exposed portions of the body should avoid excessive exposure to either natural or artificial sunlight (including tanning booths, sun lamps, etc.).

Carcinogenesis, Mutagenesis, Impairment of Fertility

When calcipotriene was applied topically to mice for up to 24 months at dosages of 3, 10 and 30 mcg/kg/day (corresponding to 9, 30 and 90 mcg/m^2/day), no significant changes in tumor incidence were observed when compared to control. In a study in which albino hairless mice were exposed to both UVR and topically applied calcipotriene, a reduction in the time required for UVR to induce the formation of skin tumors was observed (statistically significant in males only), suggesting that calcipotriene may enhance the effect of UVR to induce skin tumors. Patients that apply calcipotriene cream to exposed portions of the body should avoid excessive exposure to either natural or artificial sunlight (including tanning booths, sun lamps, etc.). Physicians may wish to limit or avoid use of phototherapy in patients that use calcipotriene cream.

Calcipotriene did not elicit any mutagenic effects in an Ames mutagenicity assay, a mouse lymphoma TK locus assay, a human lymphocyte chromosome aberration assay, or in a micronucleus assay conducted in mice.

Studies in rats at doses up to 54 mcg/kg/day (324 mcg/m^2/day) of calcipotriene indicated no impairment of fertility or general reproductive performance.

Pregnancy

Teratogenic Effects

Studies of teratogenicity were done by the oral route where bioavailability is expected to be approximately 40 to 60% of the administered dose. Increased rabbit maternal and fetal toxicity was noted at 12 mcg/kg/day (132 mcg/m^2/day). Rabbits administered 36 mcg/kg/day (396 mcg/m^2/day) resulted in fetuses with a significant increase in the incidences of pubic bones, forelimb phalanges, and incomplete bone ossification. In a rat study, oral doses of 54 mcg/kg/day (318 mcg/m^2/day) resulted in a significantly higher incidence of skeletal abnormalities consisting primarily of enlarged fontanelles and extra ribs. The enlarged fontanelles are most likely due to calcipotriene's effect upon calcium metabolism. The maternal and fetal calculated no-effect exposures in the rat (43.2 mcg/m^2/day) and rabbit (17.6 mcg/m^2/day) studies are approximately equal to the expected human systemic exposure level (18.5 mcg/m^2/day) from dermal application. There are no adequate and well-controlled studies in pregnant women. Therefore, calcipotriene cream should be used during pregnancy only if the potential benefit justifies the potential risk to the fetus.

Nursing Mothers

There is evidence that maternal 1,25-dihydroxy vitamin D3 (calcitriol) may enter the fetal circulation, but it is not known whether it is excreted in human milk. The systemic disposition of calcipotriene is expected to be similar to that of the naturally occurring vitamin. Because many drugs are excreted in human milk, caution should be exercised when calcipotriene cream is administered to a nursing woman.

Pediatric Use

Safety and effectiveness of calcipotriene cream in pediatric patients have not been established. Because of a higher ratio of skin surface area to body mass, pediatric patients are at greater risk than adults of systemic adverse effects when they are treated with topical medication.

Geriatric Use

Of the total number of patients in clinical studies of calcipotriene cream, approximately 15% were 65 or older, while approximately 3% were 75 and over. There were no significant differences in adverse events for subjects over 65 years compared to those under 65 years of age. However, the greater sensitivity of older individuals cannot be ruled out.

ADVERSE REACTIONS

Clinical Trials Experience

In controlled clinical trials, the most frequent adverse experiences reported for calcipotriene cream, 0.005% were cases of skin irritation, which occurred in approximately 10 to 15% of patients. Rash, pruritus, dermatitis and worsening of psoriasis were reported in 1 to 10% of patients.

Postmarketing Experience

Because these reactions are reported voluntarily from a population of uncertain size, it is not always possible to reliably estimate their frequency or establish a causal relationship to drug exposure.

The following adverse reactions associated with the use of calcipotriene cream have been identified post-approval: contact dermatitis, including allergic contact dermatitis.

To report SUSPECTED ADVERSE REACTIONS, contact Glenmark Pharmaceuticals Inc., USA at 1 (888) 721-7115 or FDA at 1-800-FDA-1088 or www.fda.gov/medwatch.

OVERDOSAGE

Topically applied calcipotriene can be absorbed in sufficient amounts to produce systemic effects. Elevated serum calcium has been observed with excessive use of topical calcipotriene. If elevation in serum calcium should occur, discontinue treatment until normal calcium levels are restored (see PRECAUTIONS).

DOSAGE AND ADMINISTRATION

Apply a thin layer of calcipotriene cream to the affected skin twice daily and rub in gently and completely. The safety and efficacy of calcipotriene cream have been demonstrated in patients treated for eight weeks.

HOW SUPPLIED

Calcipotriene cream USP, 0.005% is available in:

60 gram tube (1 tube per carton), NDC 68462-501-65

120 gram tube (1 tube per carton), NDC 68462-501-66

STORAGE

Store at 20°C to 25°C (68°F to 77°F); excursions permitted to 15°C to 30°C (59°F to 86°F) [see USP Controlled Room Temperature]. Do not freeze.

Distributed by:

Glenmark Pharmaceuticals Inc., USA

Elmwood Park, NJ 07407

Questions? 1 (888) 721-7115
www.glenmarkpharma-us.com

March 2025

PACKAGE/LABEL PRINCIPAL DISPLAY PANEL-60 gm Carton

NDC 68462-501-65

Calcipotriene Cream USP, 0.005%

60 gm Carton label

PACKAGE/LABEL PRINCIPAL DISPLAY PANEL-120 gm Carton

NDC 68462-501-66

Calcipotriene Cream USP, 0.005%

120 gm Carton Label